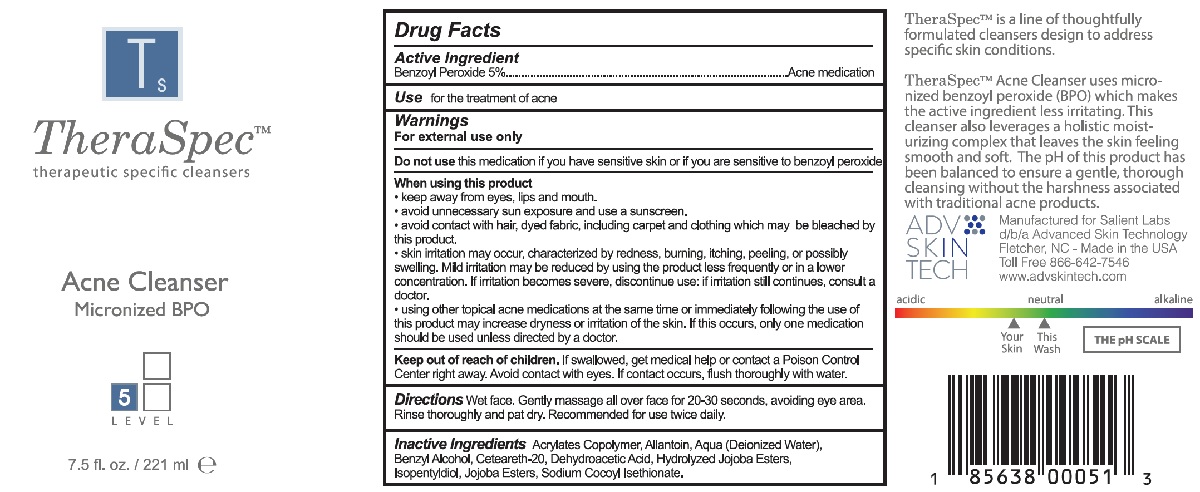 DRUG LABEL: TheraSpec
NDC: 52205-003 | Form: SOAP
Manufacturer: Salient Labs, LLC
Category: otc | Type: HUMAN OTC DRUG LABEL
Date: 20191116

ACTIVE INGREDIENTS: BENZOYL PEROXIDE 5 g/100 mL
INACTIVE INGREDIENTS: BUTYL ACRYLATE/METHYL METHACRYLATE/METHACRYLIC ACID COPOLYMER (18000 MW); HYDROLYZED JOJOBA ESTERS (ACID FORM); ALLANTOIN; WATER; SODIUM COCOYL ISETHIONATE; DEHYDROACETIC ACID; ISOPENTYLDIOL; JOJOBA OIL, RANDOMIZED; BENZYL ALCOHOL; POLYOXYL 20 CETOSTEARYL ETHER

TheraSpec Acne Cleanser

Active Ingredient

Benzoyl Peroxide 5%

PURPOSE

Acne medication

Use

for the treatment of acne

Warnings

For external use only

Do not use this medication if you have very sensitive skin or if you are sensitive to benzoyl peroxide

When using this product

- keep away from eyes, lips and mouth
- avoid unnecessary sun exposure and use a sunscreen
- avoid contact with hair, dyed fabric, including carpet and clothing which may be bleached by this product
- skin irritation may occur, characterized by redness, burning, itching, peeling, or possibly swelling. Mild irritation may be reduced by using the product less frequently or in a lower concentration. lf irritation becomes severe, discontinue use: if irritation still continues, consult a doctor.
- using other topical acne medications at the same time or immediately following the use of this product may increase dryness or irritation of the skin. If this occurs, only one medication should be used unless directed by a doctor.

Keep out of reach of children. If swallowed, get medical help or contact a Poison Control Center right away. Avoid contact with eyes. If contact occurs, flush thoroughly with water.

DOSAGE AND ADMINISTRATION

Directions Wet face. Gently massage all over face for 20-30 seconds, avoiding eye area. Rinse thoroughly and pat dry. Recommended for use twice daily.

INACTIVE INGREDIENT

Inactive Ingredients Acrylates Copolymer, Allantoin, Aqua (Deionized Water), Benzyl Alcohol, Ceteareth-20, Dehydroacetic Acid, Hydrolyzed Jojoba Esters, lsopentyldiol, Jojoba Esters, Sodium Cocyl lsethionate.

PACKAGE LABEL

TheraSpec

Acne Cleanser

Principal Display Panel

221 ml

NDC: 52205-003-00